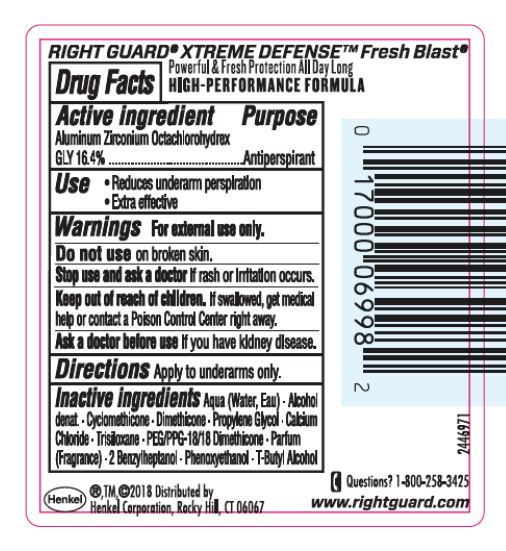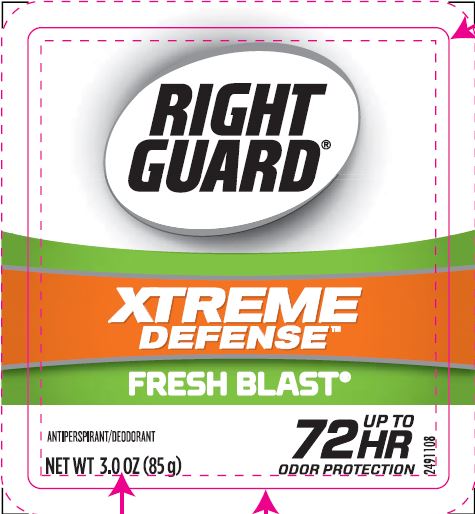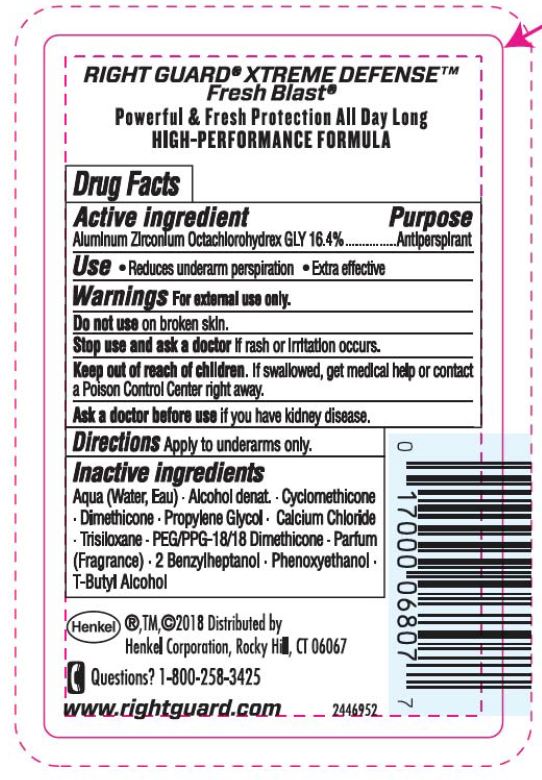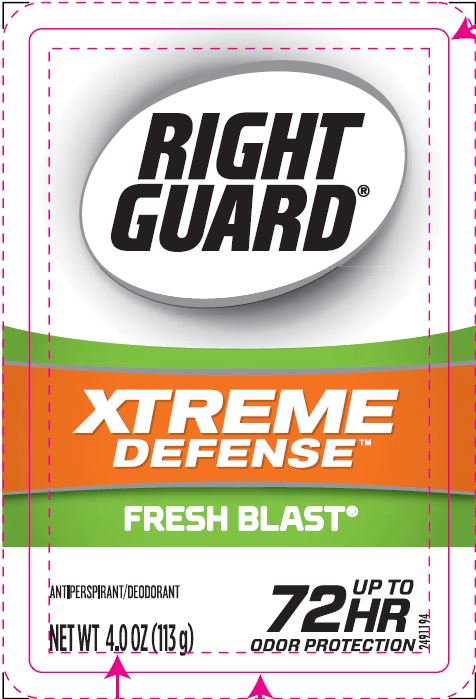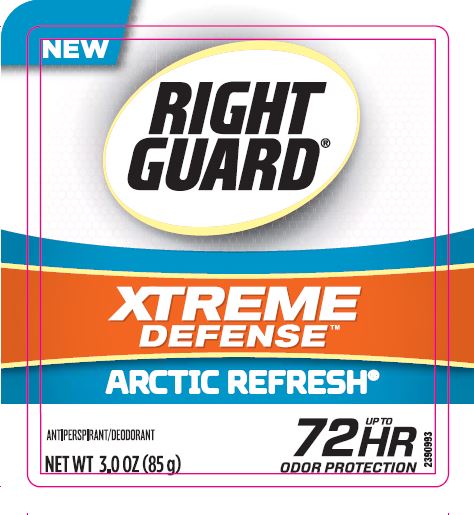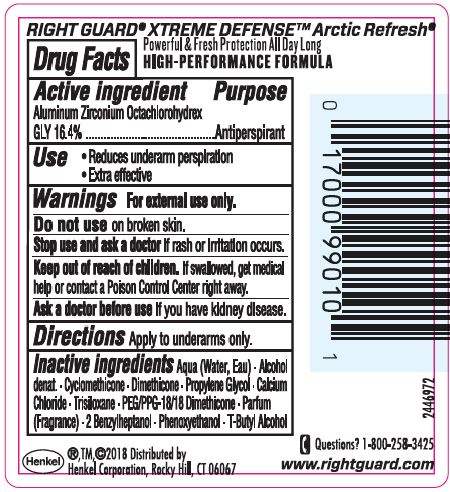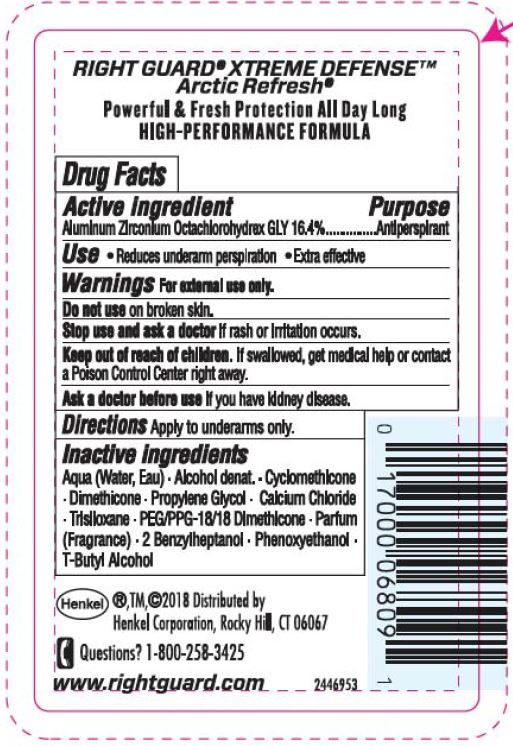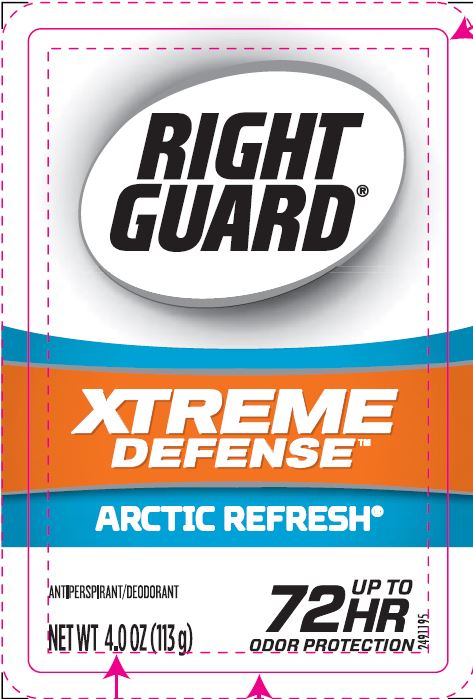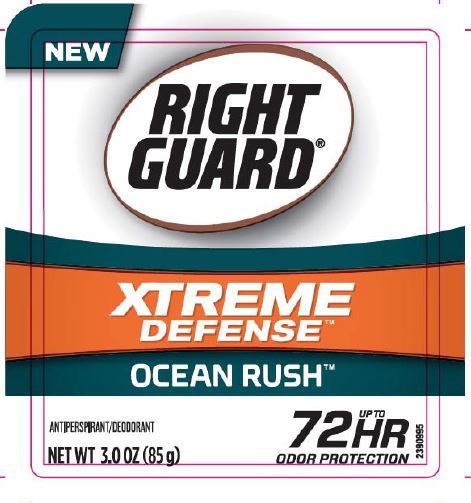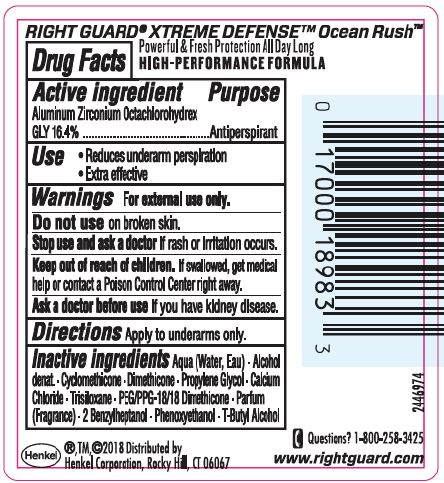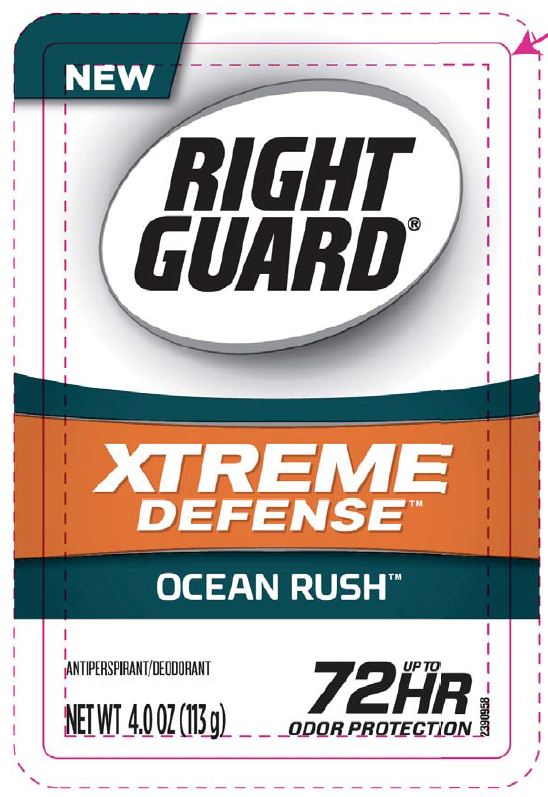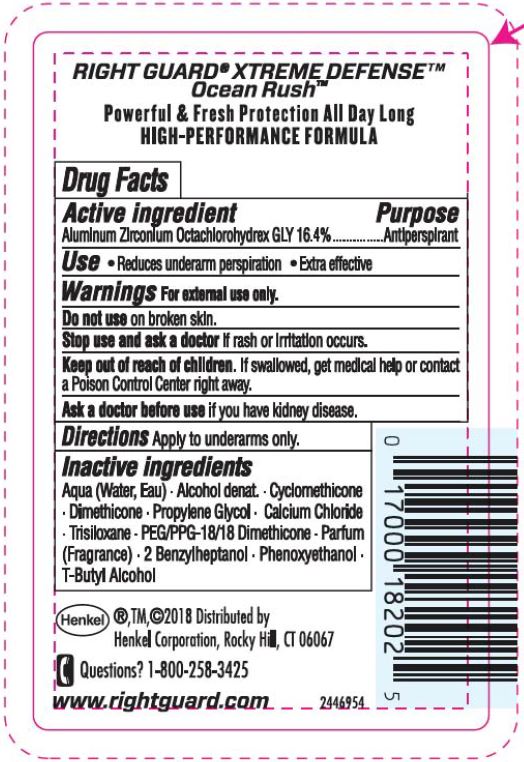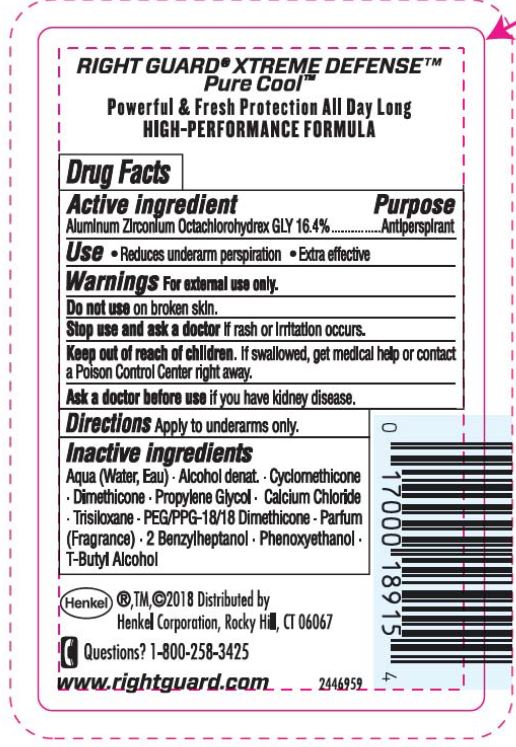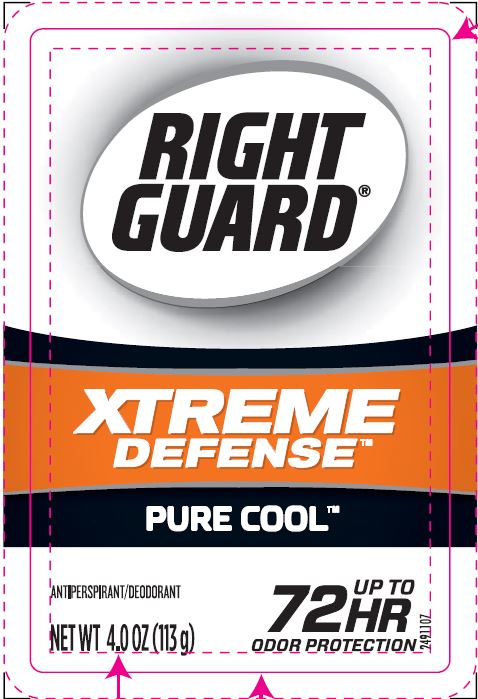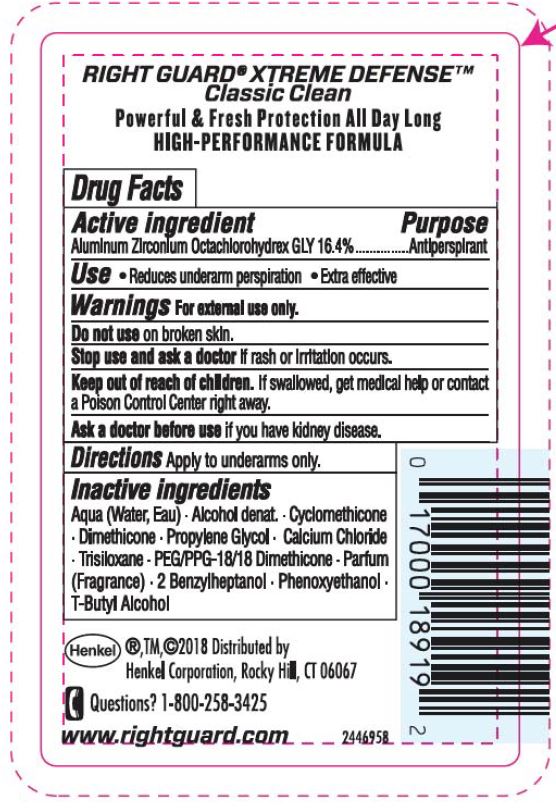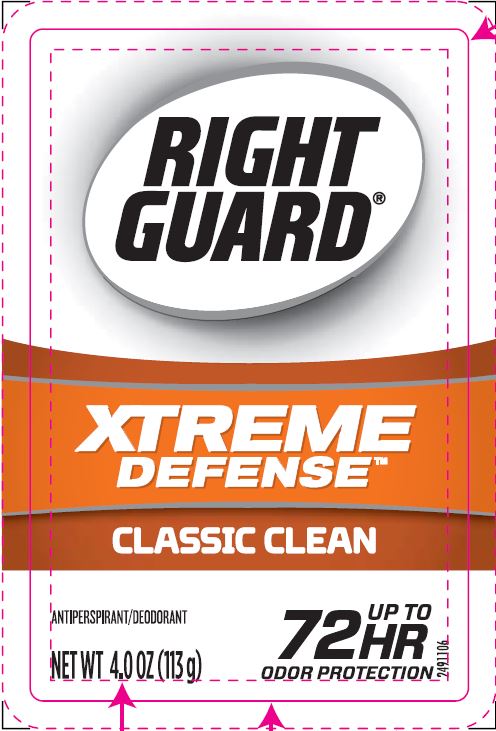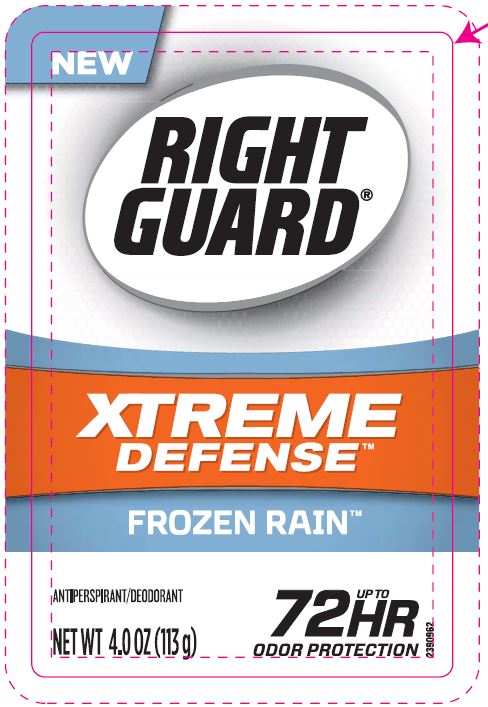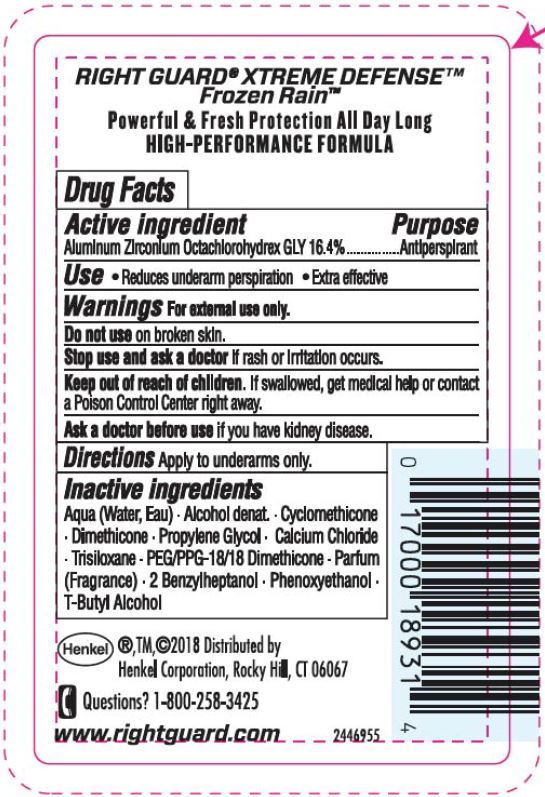 DRUG LABEL: Right Guard Antiperspirant
NDC: 54340-854 | Form: GEL
Manufacturer: Henkel Corporation
Category: otc | Type: HUMAN OTC DRUG LABEL
Date: 20201029

ACTIVE INGREDIENTS: ALUMINUM ZIRCONIUM OCTACHLOROHYDREX GLY 16.4 g/100 g
INACTIVE INGREDIENTS: WATER 40.04 g/100 g

Right Guard Antiperspirant Gel - Xtreme

Active ingredient

Aluminum Zirconium Octachlorohydrex GLY 16.4%

Purpose

Antiperspirant

Use

• Reduces underarm perspiration

• Extra effective

Warnings

For external use only.

Do not use

on broken skin.

Stop use and ask a doctor

if rash or irritation occurs.

Keep out of reach of children.

If swallowed, get medical help or contact a Poison Control Center right away.

Ask a doctor before use

if you have kidney disease.

Directions

Apply to underarms only.

Inactive ingredients

Aqua (Water, Eau) • Alcohol Denat. • Cyclomethicone • Dimethicone • Propylene Glycol • Calcium Chloride • Trisiloxane • PEG/PPG-18/18 Dimethicone •Parfum (Fragrance) • 2 Benzylheptanol • Phenoxyethanol • T-Butyl Alcohol

Questions? 1-800-258-3425